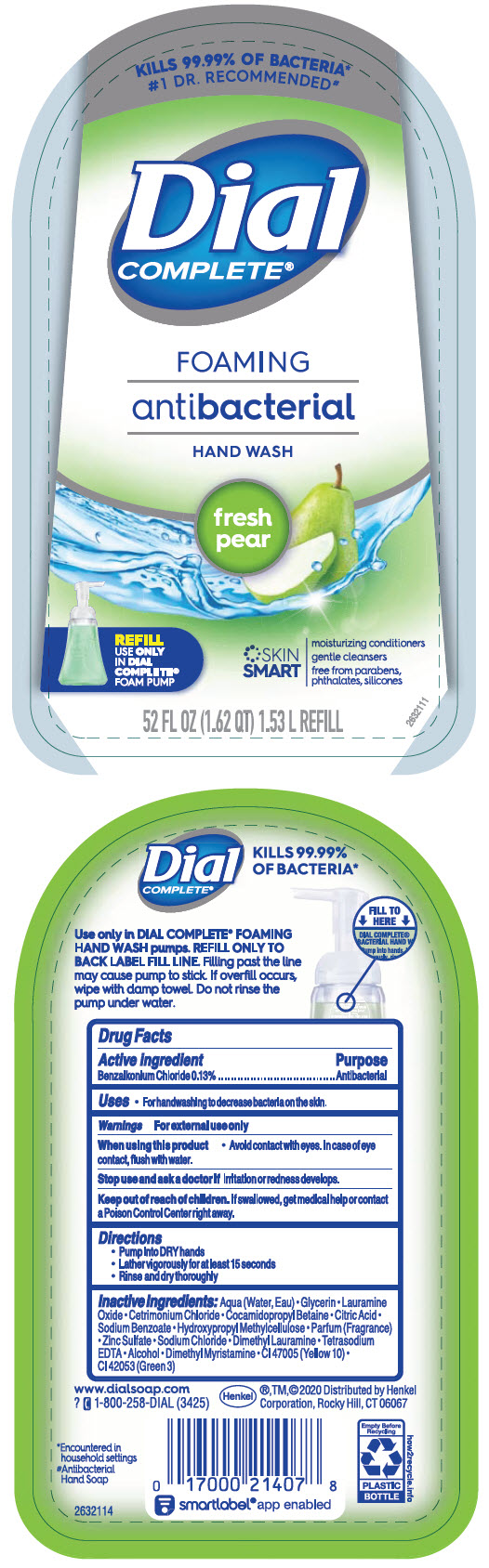 DRUG LABEL: Dial Complete Antibacterial Foaming Hand Wash 
NDC: 69560-567 | Form: SOLUTION
Manufacturer: MID-CONTINENT PACKAGING, INC.
Category: otc | Type: HUMAN OTC DRUG LABEL
Date: 20211216

ACTIVE INGREDIENTS: Benzalkonium Chloride 1.3 mg/1 mL
INACTIVE INGREDIENTS: Water; Lauramine Oxide; Cetrimonium Chloride; GLYCERIN; Cocamidopropyl Betaine; ANHYDROUS CITRIC ACID; Hypromellose, Unspecified; Sodium Benzoate; Zinc Sulfate Heptahydrate; Edetate Sodium; Dimethyl Lauramine; Alcohol; Dimethyl Myristamine; D&C YELLOW NO. 10; FD&C GREEN NO. 3

Dial Complete® Antibacterial Foaming Hand Wash
Fresh Pear

Drug Facts

Active ingredient

Benzalkonium Chloride 0.13%

Purpose

Antibacterial

Uses

- For handwashing to decrease bacteria on the skin.

Warnings

For external use only

When using this product

- Avoid contact with eyes. In case of eye contact, flush with water.

Stop use and ask a doctor if irritation or redness develops.

Keep out of reach of children. If swallowed, get medical help or contact a Poison Control Center right away.

Directions

- Pump into DRY hands
- Lather vigorously for at least 15 seconds
- Rinse and dry thoroughly

Inactive ingredients

Aqua (Water, Eau) • Glycerin • Lauramine Oxide • Cetrimonium Chloride • Cocamidopropyl Betaine • Citric Acid • Sodium Benzoate • Hydroxypropyl Methylcellulose • Parfum (Fragrance) • Zinc Sulfate • Sodium Chloride • Dimethyl Lauramine • Tetrasodium EDTA • Alcohol • Dimethyl Myristamine • CI 47005 (Yellow 10) • CI 42053 (Green 3)

Distributed by Henkel Corporation, Rocky Hill, CT 06067

PRINCIPAL DISPLAY PANEL - 1.53 L Bottle Label

KILLS 99.99% OF BACTERIA*
#1 DR. RECOMMENDED#

Dial
COMPLETE®

FOAMING

antibacterial

HAND WASH

fresh
pear

REFILL
USE ONLY
IN DIAL
COMPLETE®
FOAM PUMP

SKIN
SMART

moisturizing conditioners

gentle cleansers

free from parabens,
phthalates, silicones

52 FL OZ (1.62 QT) 1.53 L REFILL

2632111